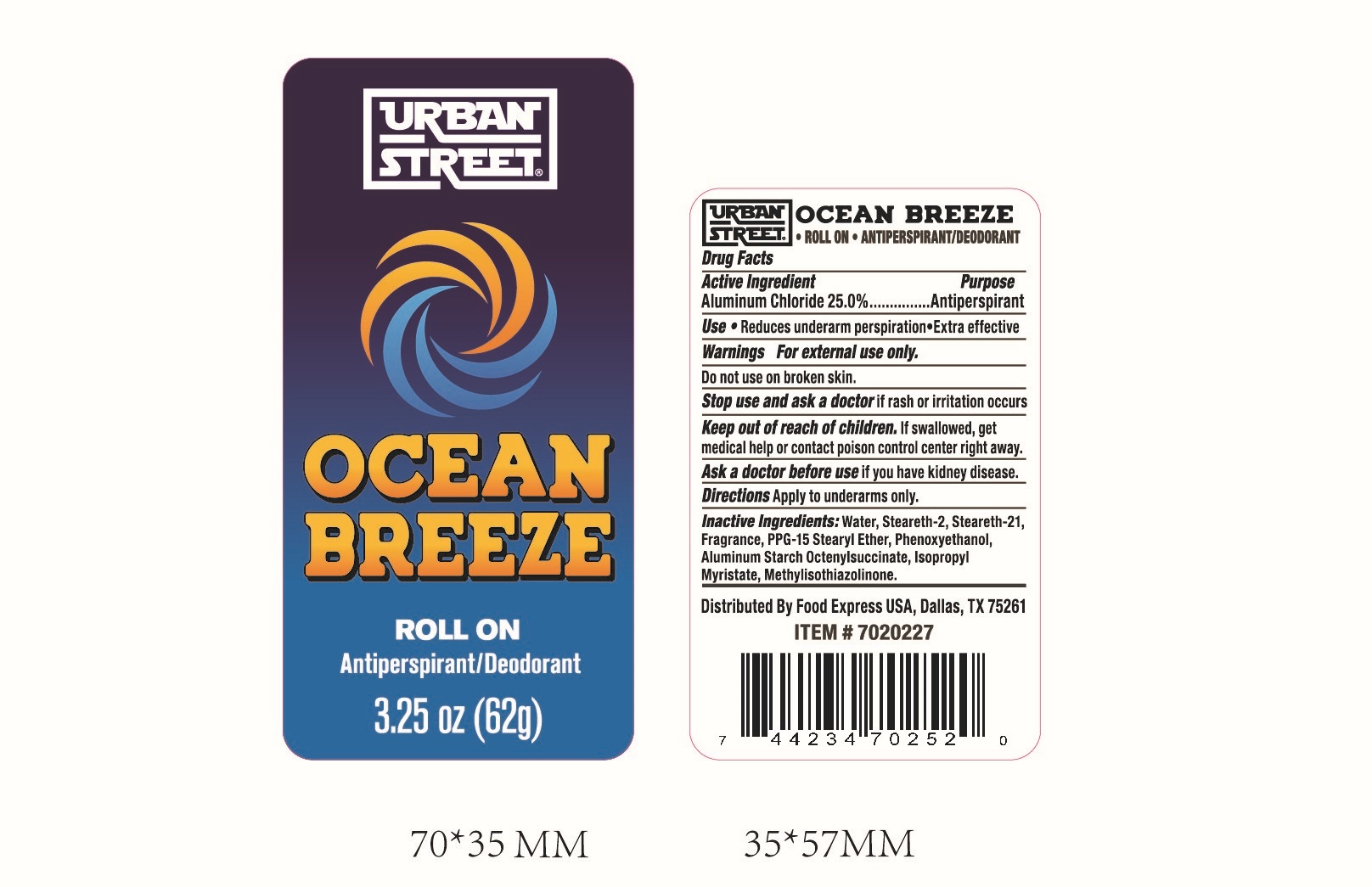 DRUG LABEL: Urban Street Ocean Breeze
NDC: 22431-227 | Form: STICK
Manufacturer: Blue Cross Laboratories LLC
Category: otc | Type: HUMAN OTC DRUG LABEL
Date: 20210708

ACTIVE INGREDIENTS: ALUMINUM CHLORIDE 250 mg/1 g
INACTIVE INGREDIENTS: STEARETH-21; PPG-15 STEARYL ETHER; PHENOXYETHANOL; METHYLISOTHIAZOLINONE; FRAGRANCE CLEAN ORC0600327; WATER; STEARETH-2; ALUMINUM STARCH OCTENYLSUCCINATE; ISOPROPYL MYRISTATE

Active Ingredient

Aluminum Chloride 25.0%

Purpose

Antiperspirant

Use

Reduces underarm perspiration. Extra effective

Warnings

For external use only

Do not use on broken skin.

Stop use and ask a doctor if rash or irritation occurs

Keep out of reach of children. If swallowed, get medical help or contact poison control center right away.

Ask a doctor before use if you have kidney disease.

Directions

Apply to underarms only.

Inactive Ingredients:

Water, Steareth-2, Steareth-31, Fragrance, PPF-15 Stearyl Ether, Phenoxyethanol, Aluminum Starch Octenylsuccinate, Isopropyl Myristate, Methylisothiazolinone

PACKAGE LABEL

Urban Street

Ocean Breeze

Roll On

Antiperspirant/Deodorant

3.25 fl. oz. (96.1 ml)